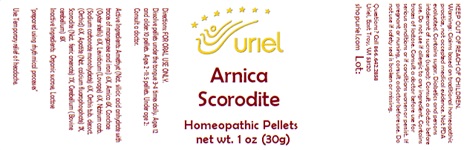 DRUG LABEL: Arnica Scorodite
NDC: 48951-1156 | Form: PELLET
Manufacturer: Uriel Pharmacy Inc.
Category: homeopathic | Type: HUMAN OTC DRUG LABEL
Date: 20240115

ACTIVE INGREDIENTS: OSTREA EDULIS SHELL 6 [hp_X]/1 1; LEVISTICUM OFFICINALE ROOT 6 [hp_X]/1 1; SODIUM CARBONATE 6 [hp_X]/1 1; ORCHIS MASCULA TUBER 6 [hp_X]/1 1; FLUORAPATITE 7 [hp_X]/1 1; FERROUS ARSENATE 7 [hp_X]/1 1; BOS TAURUS CEREBELLUM 8 [hp_X]/1 1; SILICON DIOXIDE 6 [hp_X]/1 1; ARNICA MONTANA 6 [hp_X]/1 1
INACTIVE INGREDIENTS: SUCROSE; LACTOSE

Arnica Scorodite

INDICATIONS AND USAGE

Directions: FOR ORAL USE ONLY.

DOSAGE AND ADMINISTRATION

Dissolve pellets under the tongue 3-4
times daily. Ages 12 and older: 10 pellets.
Ages 2-11: 5 pellets. Under age 2: Consult
a doctor.

ACTIVE INGREDIENT

Active Ingredients: Amethyst (Nat. silicic acid anhydrate with traces of manganese and iron) 6X, Arnica 6X, Conchae (Oyster shells) 6X, Levisticum (Lovage) 6X, Natrium carb. (Sodium carbonate monohydrate) 6X, Orchis tub. decoct. (Orchid) 6X, Apatite (Nat. calcium fluorophosphate) 7X, Scorodite (Nat. ferric arsenate) 7X, Cerebellum (Bovine cerebellum) 8X

Inactive Ingredients: Sucrose, Lactose

"prepared using rhythmical processes"

PURPOSE

Use: Temporary relief of headache.

KEEP OUT OF REACH OF CHILDREN.

WARNINGS

Warnings: Claims based on traditional homeopathic practice, not accepted medical evidence. Not FDA evaluated. Contains sugar. Diabetics and persons intolerant of sucrose (sugar): Consult a doctor before use. Do not use if allergic to any ingredient. Contains traces of lactose. Consult a doctor before use for serious conditions or if conditions worsen or persist. If pregnant or nursing, consult a doctor before use. Do not use if safety seal is broken or missing.

Questions? Call 866.642.2858
Uriel, East Troy, WI 53120
shopuriel.com